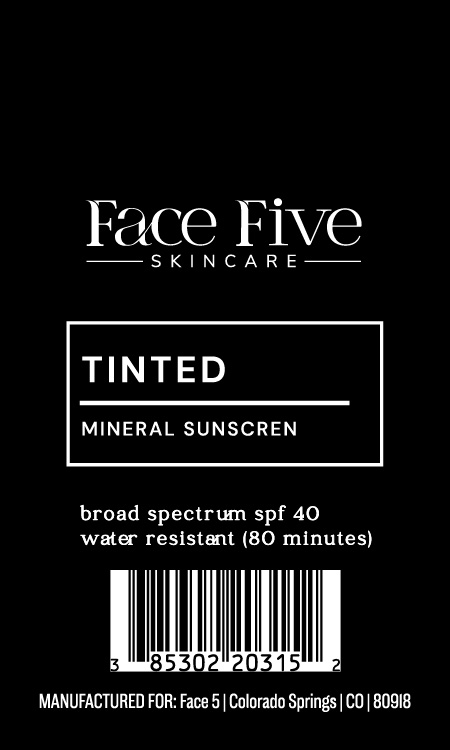 DRUG LABEL: Tinted Mineral Sunscreen
NDC: 85302-203 | Form: CREAM
Manufacturer: Face 5, LLC
Category: otc | Type: HUMAN OTC DRUG LABEL
Date: 20251208

ACTIVE INGREDIENTS: TITANIUM DIOXIDE 80 mg/1 g; ZINC OXIDE 38 mg/1 g
INACTIVE INGREDIENTS: ALUMINA; DIMETHICONE/VINYL DIMETHICONE CROSSPOLYMER (SOFT PARTICLE); CYCLOHEXASILOXANE; DIMETHICONE CROSSPOLYMER; CI 77491; CYCLOPENTASILOXANE; LAURYL PEG/PPG-18/18 METHICONE; DIMETHICONOL (2000 CST); PEG-10 DIMETHICONE (600 CST); DIMETHICONE; HYDROGEN DIMETHICONE (20 CST); ALPHA-TOCOPHEROL ACETATE; TETRAHEXYLDECYL ASCORBATE

Active Ingredients:

Titanium Dioxide 8% Zinc Oxide 3.8%

Purpose:

Sunscreen

Warning:

- For external use only
- Keep out of reach of children

Warnings:

- For external use only
- Keep out of reach of children

Directions:

Apply liberally 15 minute before sun exposure

INACTIVE INGREDIENT

Alumina, Cyclohexasiloxane, Cyclopentasiloxane, Dimethicone, Dimethicone Crosspolymer, Dimethicone/Vinyl Dimethicone Crosspolymer, Dimethiconol, Iron Oxide (CI 77491), Lauryl PEG/PPG-18/18 Methicone, Hydrogen Dimethicone, PEG-10 Dimethicone, Tetrahexyldecyl Ascorbate, Tocopheryl Acetate

OTHER SAFETY INFORMATION

SAMPLE NOT FOR RESALE

Warning:

Keep out of reach of children